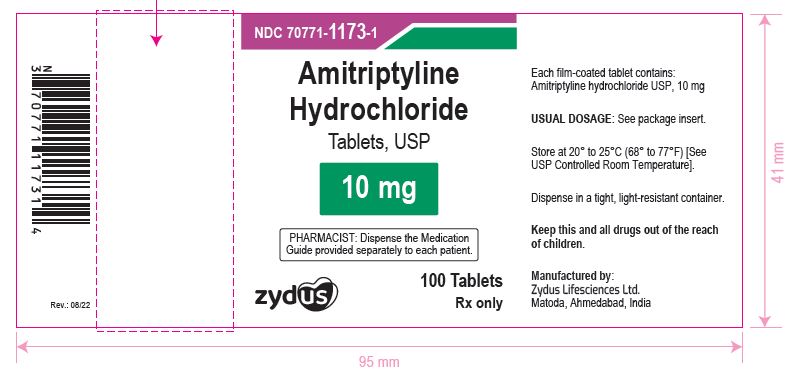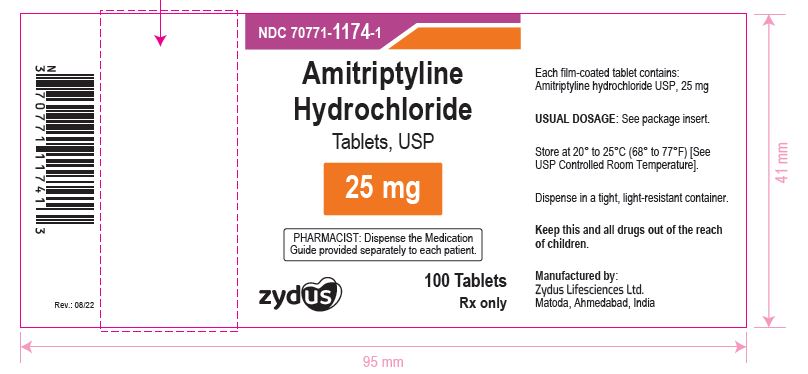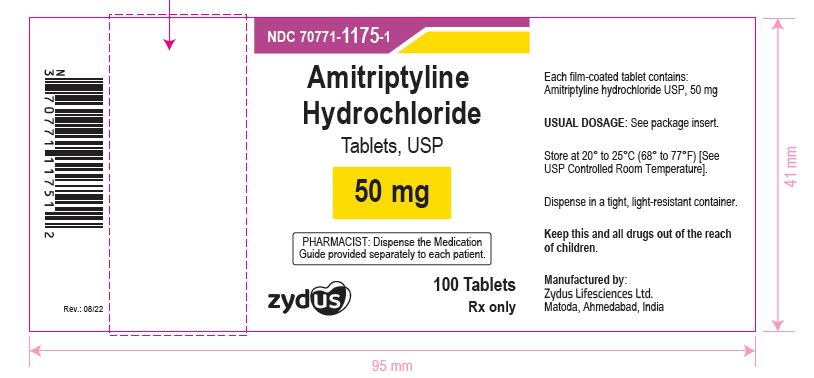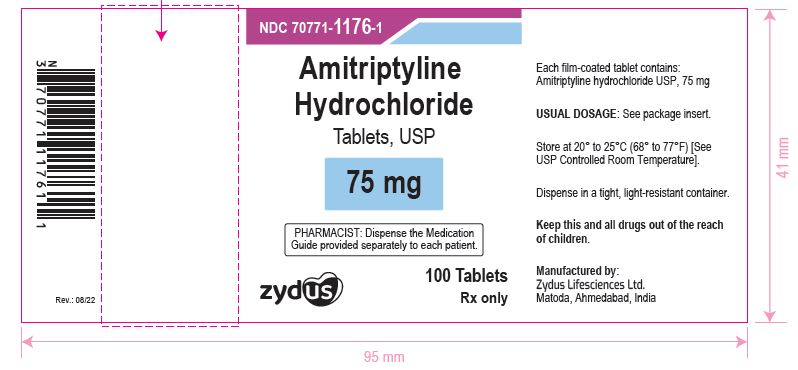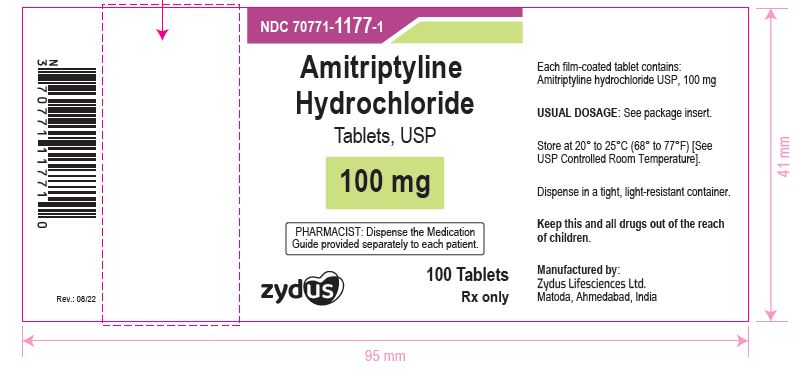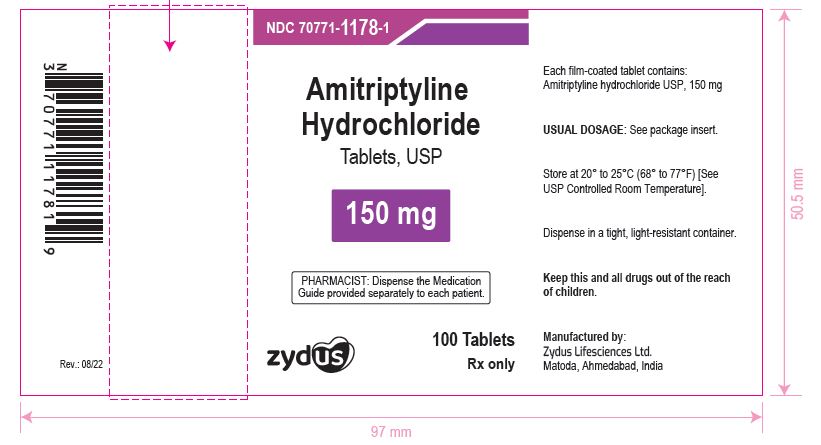 DRUG LABEL: Amitriptyline Hydrochloride
NDC: 70771-1173 | Form: TABLET, FILM COATED
Manufacturer: Zydus Lifesciences Limited
Category: prescription | Type: HUMAN PRESCRIPTION DRUG LABEL
Date: 20251004

ACTIVE INGREDIENTS: AMITRIPTYLINE HYDROCHLORIDE 10 mg/1 1
INACTIVE INGREDIENTS: LACTOSE MONOHYDRATE; CELLULOSE, MICROCRYSTALLINE; STARCH, CORN; CROSCARMELLOSE SODIUM; SILICON DIOXIDE; MAGNESIUM STEARATE; HYPROMELLOSE 2910 (6 MPA.S); POLYETHYLENE GLYCOL 8000; TITANIUM DIOXIDE; TALC

Amitriptyline Hydrochloride Tablets, USP

PACKAGE LABEL.PRINCIPAL DISPLAY PANEL

NDC 70771-1173-1 in bottle of 100 Tablets

Amitriptyline Hydrochloride Tablets USP, 10 mg

Rx only

100 Tablets

NDC 70771-1174-1 in bottle of 100 Tablets

Amitriptyline Hydrochloride Tablets USP, 25 mg

Rx only

100 Tablets

NDC 70771-1175-1 in bottle of 100 Tablets

Amitriptyline Hydrochloride Tablets USP, 50 mg

Rx only

100 Tablets

NDC 70771-1176-1 in bottle of 100 Tablets

Amitriptyline Hydrochloride Tablets USP, 75 mg

Rx only

100 Tablets

NDC 70771-1177-1 in bottle of 100 Tablets

Amitriptyline Hydrochloride Tablets USP, 100 mg

Rx only

100 Tablets

NDC 70771-1178-1 in bottle of 100 Tablets

Amitriptyline Hydrochloride Tablets USP, 150 mg

Rx only

100 Tablets